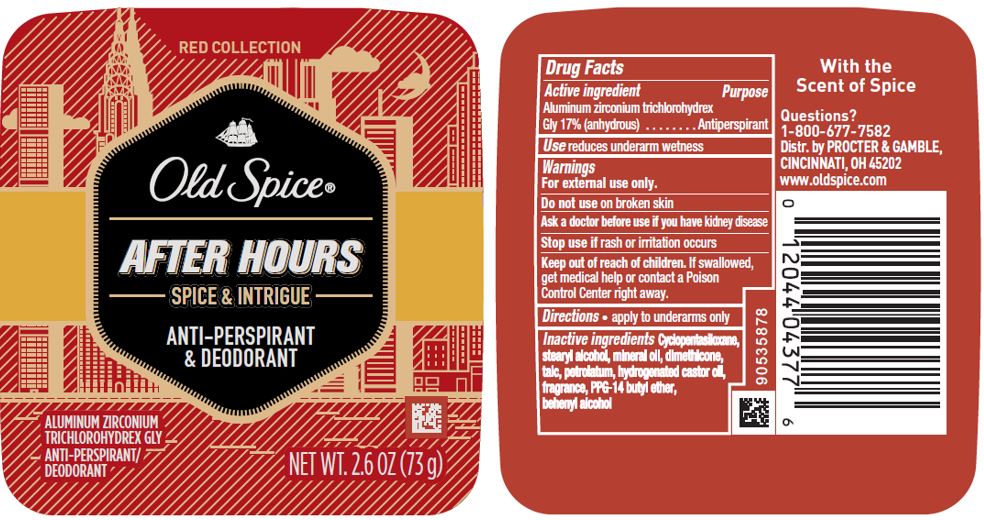 DRUG LABEL: Old Spice Red Collection After Hours
NDC: 69423-397 | Form: STICK
Manufacturer: The Procter & Gamble Manufacturing Company
Category: otc | Type: HUMAN OTC DRUG LABEL
Date: 20200330

ACTIVE INGREDIENTS: ALUMINUM ZIRCONIUM TRICHLOROHYDREX GLY 17 g/100 g
INACTIVE INGREDIENTS: CYCLOMETHICONE 5; STEARYL ALCOHOL; PPG-14 BUTYL ETHER; HYDROGENATED CASTOR OIL; PETROLATUM; TALC; MINERAL OIL; DOCOSANOL; DIMETHICONE

Old Spice Red Collection After Hours IS

Drug Facts

Active ingredient

Aluminum zirconium trichlorohydrex Gly 17% (anhydrous)

Purpose

Antiperspirant

Use

reduces underarm wetness

Warnings

For external use only.

Do not use on broken skin

Ask a doctor before use if you have kidney disease

Stop use if rash or irritation occurs

Keep out of reach of children. If swallowed, get medical help or contact a Poison Control Center right away.

Directions

- apply to underarms only

Inactive ingredients

Cyclopentasiloxane, stearyl alcohol, mineral oil, dimethicone, talc, petrolatum, hydrogenated castor oil, fragrance, PPG-14 butyl ether, behenyl alcohol

Questions?

1-800-677-7582

Dist. by PROCTER & GAMBLE,
CINCINNATI, OH 45202.

PRINCIPAL DISPLAY PANEL 73 g CANISTER LABEL

RED COLLECTION

Old Spice

AFTER HOURS

SPICE & INTRIGUE

ANTI-PERSPIRANT

& DEODORANT

ALUMINUM ZIRCONIUM

TRICHLOROHYDREX GLY

ANTI-PERSPIRANT

/DEODORANT

NET WT. 2.6 OZ (73g)